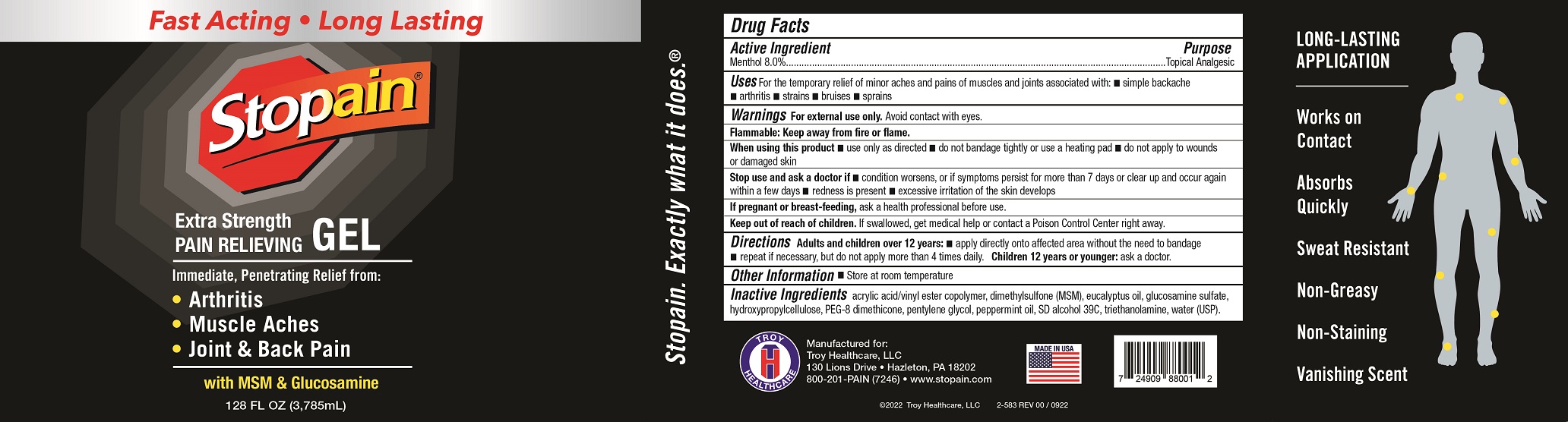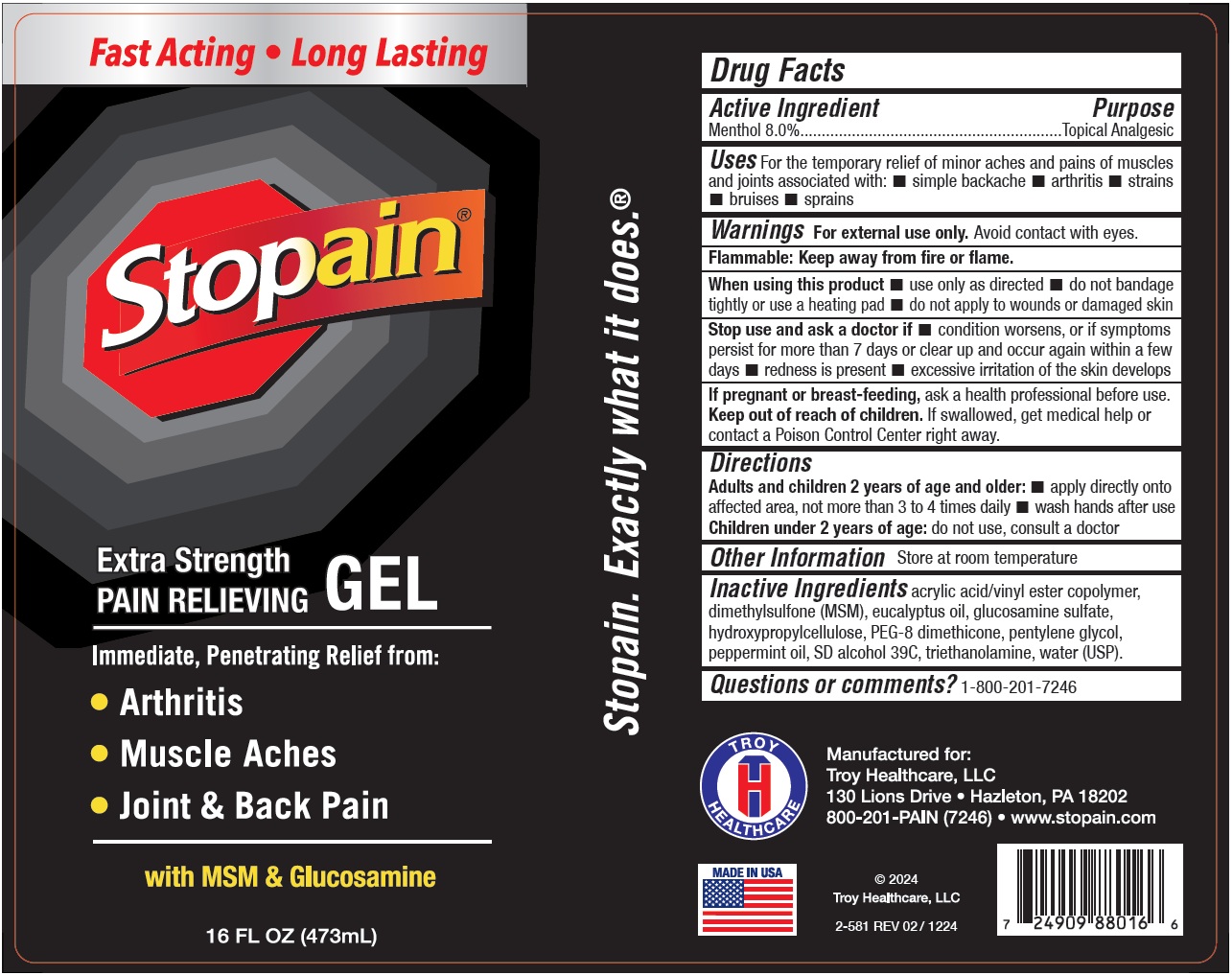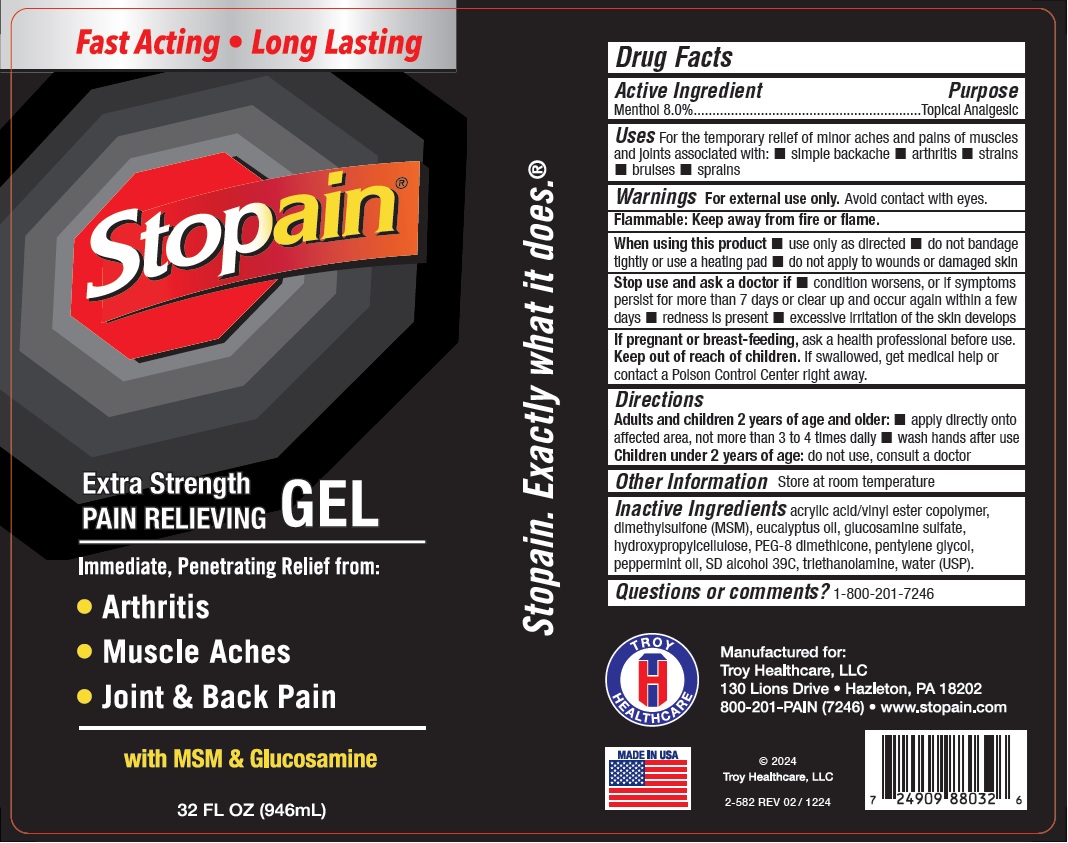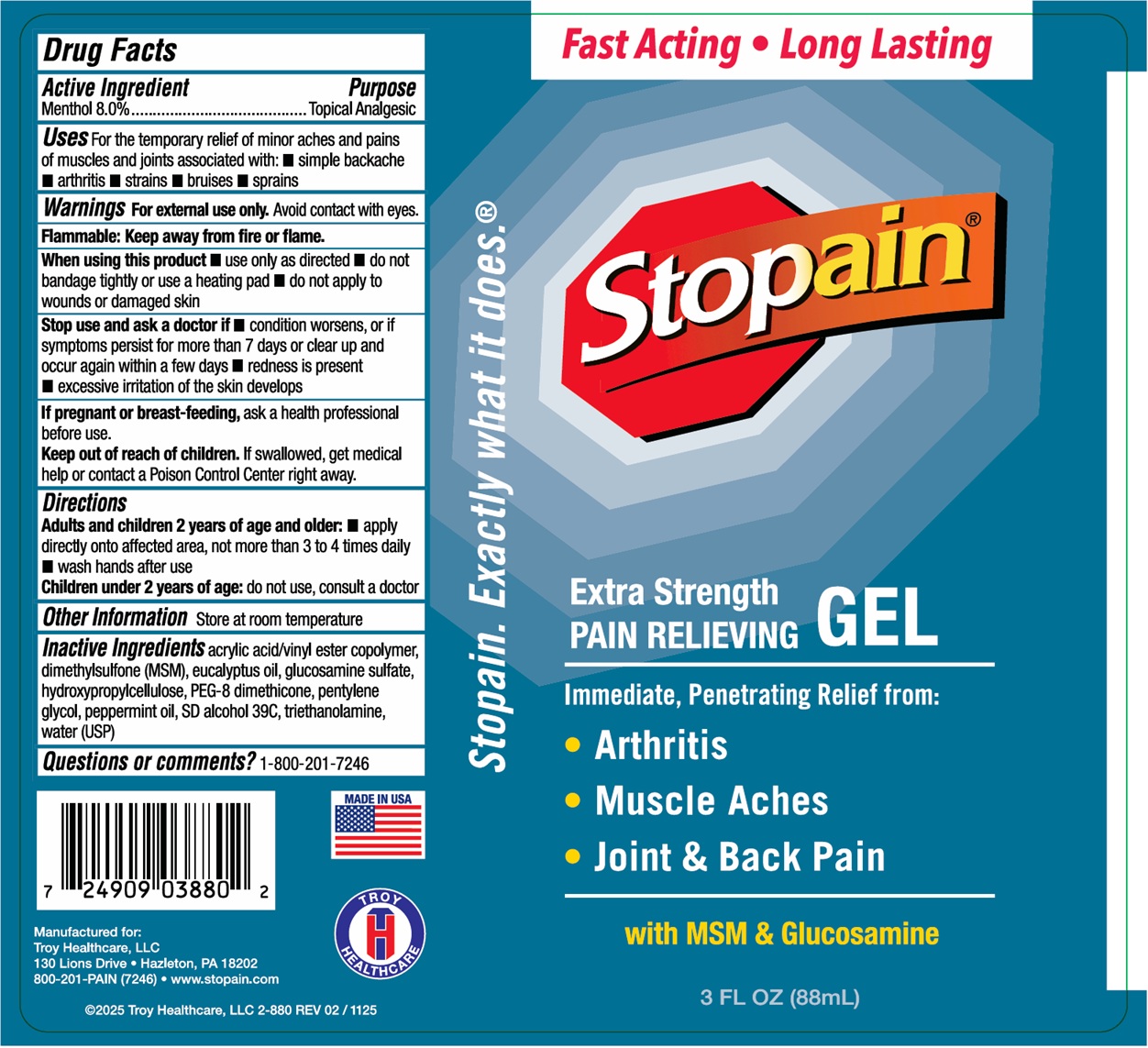 DRUG LABEL: Stopain Extra Strength Gel
NDC: 63936-8800 | Form: GEL
Manufacturer: Troy Manufacturing, Inc.
Category: otc | Type: HUMAN OTC DRUG LABEL
Date: 20251209

ACTIVE INGREDIENTS: MENTHOL 80 mg/1 mL
INACTIVE INGREDIENTS: EUCALYPTUS OIL; GLUCOSAMINE SULFATE; HYDROXYPROPYL CELLULOSE, UNSPECIFIED; PEG-8 DIMETHICONE; PENTYLENE GLYCOL; PEPPERMINT OIL; TROLAMINE; WATER; DIMETHYL SULFONE

Stopain Extra Strength Gel

Active Ingredient

Menthol 8.0%

Purpose

Topical Analgesic

Uses

For the temporary relief of minor aches and pains of muscles and joints associated with: • simple backache • arthritis • strains • bruises • sprains

Warnings

For external use only.Avoid contact with eyes

Flammable: Keep away from fire or flame.

When using this product

• use only as directed • do not bandage tightly or use a heating pad • do not apply to wounds or damaged skin

Stop use and ask a doctor if

• condition worsens, or if symptoms persist for more than 7 days or clear up and occur again wihin a few days • redness is present • excessive irritation of the skin develops

If pregnant or breast-feeding,

ask a health professional before use.

Keep out of reach of children.

If swallowed, get medical help or contact a Poison Control Center right away.

Directions

Adults and children 2 years of age and older: • apply directly onto affected area, not more than 3 to 4 times daily • wash hands after use

Children under 2 years of age:do not use, consult a doctor

Other Information

Store at room temperature

Inactive Ingredients

acrylic acid/vinyl ester copolymer, dimethylsulfone (MSM), eucalyptus oil, glucosamine sulfate, hydroxypropylcellulose, PEG-8 dimethicone, pentylene glycol, peppermint oil, SD alcohol 39C, triethanolamine, water (USP).

Questions or comments?

1-800-201-7246